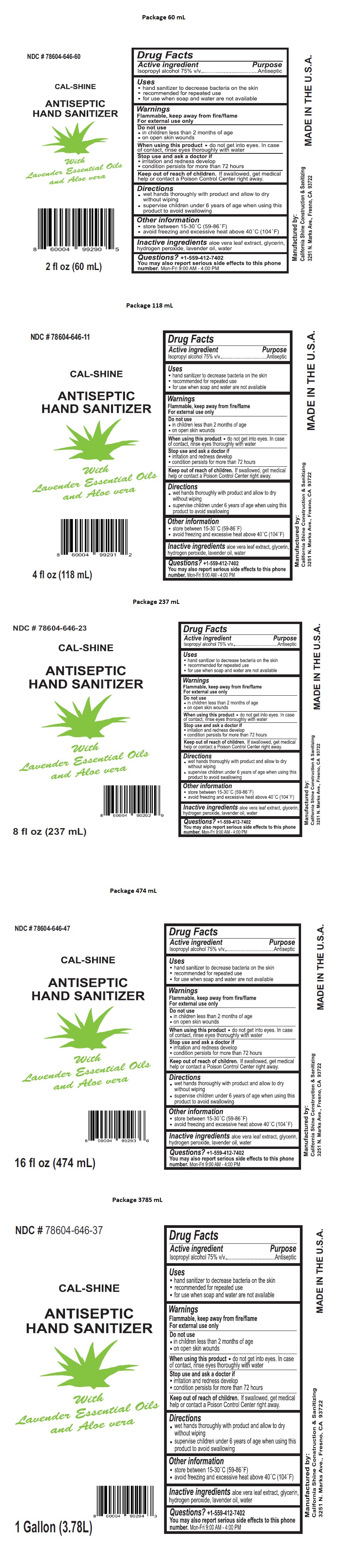 DRUG LABEL: CAL-SHINE ANTISEPTIC HAND SANITIZER
NDC: 78604-646 | Form: LIQUID
Manufacturer: California Shine Construction
Category: otc | Type: HUMAN OTC DRUG LABEL
Date: 20230112

ACTIVE INGREDIENTS: ISOPROPYL ALCOHOL 75 mL/100 mL
INACTIVE INGREDIENTS: ALOE VERA LEAF; GLYCERIN; HYDROGEN PEROXIDE; LAVENDER OIL; WATER

CAL-SHINE ANTISEPTIC HAND SANITIZER

Active ingredient

Isopropyl alcohol 75% v/v

Purpose

Antiseptic

Uses

- hand sanitizer to decrease bacteria on the skin
- recommended for repeated use
- for use when soap and water are not available

Warnings

Flammable, keep away from fire/flame

For external use only

Do not use

- in children less than 2 months of age
- on open skin wounds

When using this product • do not get into eyes. In case of contact, rinse eyes thoroughly with water

Stop use and ask a doctor if

- irritation and redness develop
- condition persists for more than 72 hours

Keep out of reach of children. If swallowed, get medical help or contact a Poison Control Center right away.

Directions

- wet hands thoroughly with product and allow to dry without wiping
- supervise children under 6 years of age when using this product to avoid swallowing

Other information

- store between 15-30°C (59-86°F)
- avoid freezing and excessive heat above 40°C (104°F)

Inactive ingredients

aloe vera leaf extract, glycerin, hydrogen peroxide, lavender oil, water

Questions? +1-559-412-7402

You may also report serious side effects to this phone number. Mon-Fri 9:00 AM - 4:00 PM

With Lavender Essential Oils and Aloe vera

Manufactured by:
California Shine Construction & Sanitizing,
3251 N Marks Ave, Fresno, CA 93722

MADE IN THE U.S.A.